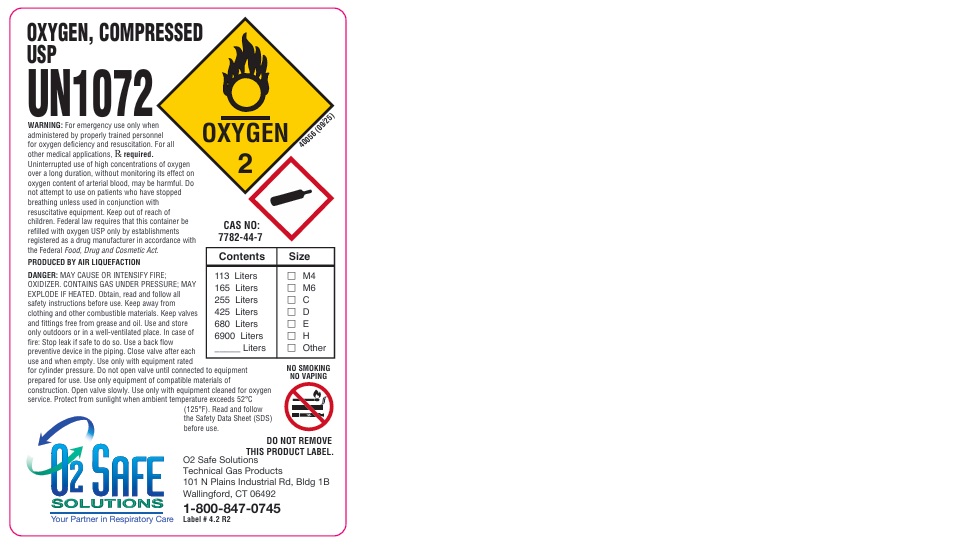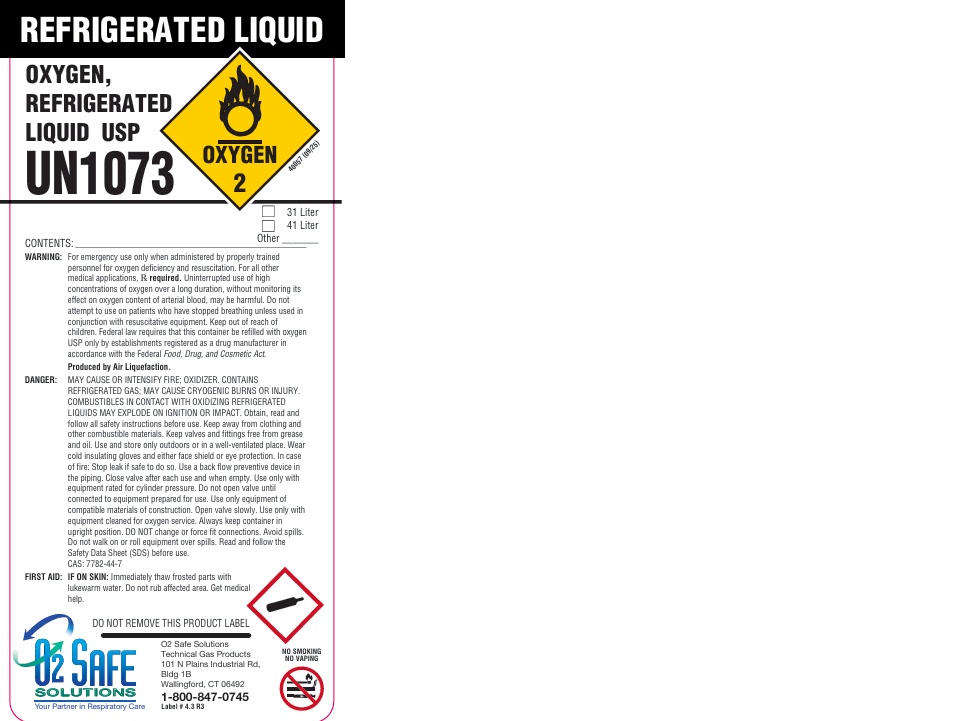 DRUG LABEL: Oxygen
NDC: 65010-011 | Form: GAS
Manufacturer: Technical Gas Products, Inc.
Category: animal | Type: PRESCRIPTION ANIMAL DRUG LABEL
Date: 20251007

ACTIVE INGREDIENTS: Oxygen 999 mL/1 L

Oxygen Label

PACKAGE LABEL

OXYGEN, COMPRESSED USP
UN1072
WARNING: For emergency use only when administered by properly trained personnel for oxygen deficiency and resuscitation. For all other applications, Rx required. Uninterrupted use of high concentrations of oxygen over a long duration, without monitoring its effect on oxygen content of arterial blood, may be harmful. Do not attempt to use on patients who have stopped breathing unless used in conjunction with resuscitative equipment. Keep out of reach of children. Federal law requires that this container be refilled with oxygen USP only by establishments registered as a drug manufacturer in accordance with the Federal Food, Drug and Cosmetic Act.
PRODUCED BY AIR LIQUEFACTION
DANGER: MAY CAUSE OR INTENSIFY FIRE; OXIDIZER. CONTAINS GAS UNDER PRESSURE; MAY EXPLODE IF HEATED. Obtain, read and follow all safety instructions before use. Keep away from clothing and other combustible materials. Keep valves and fittings free from grease and oil. Use and store only outdoors or in a well-ventilated place. In case of fire: Stop leak if safe to do so. Use a back flow preventive device in the piping. Close valve after each use and when empty. Use only with equipment rated for cylinder pressure. Do not open valve until connected to equipment prepared for use. Use only with equipment of compatible materials of construction. Open valve slowly. Use only with equipment cleaned for oxygen service. Protect from sunlight when ambient temperature exceeds 52 C (125 F). Read and follow the Safety Data Sheet (SDS) before use.
CAS NO: 7782-44-7
Contents Size
113 Liters M4
165 Liters M6
255 Liters C
425 Liters D
680 Liters E
6900 Liters H
Liters Other
NO SMOKING
NO VAPING
DO NOT REMOVE THIS PRODUCT LABEL.
O2 SAFE SOLUTIONS
Your Partner in Respiratory Care
O2 Safe Solutions
Technical Gas Products
101 N Plains Industrial Rd, Bldg 1B
Wallingford, CT 06492
1-800-847-0745

PACKAGE LABEL

REFRIGERATED LIQUID
OXYGEN, REFRIGERATED LIQUID USP
UN1073
31 Liter
41 Liter
CONTENTS: Other
WARNING: For emergency use when administered by properly trained personnel for oxygen deficiency and resuscitation. For all other medical applications, Rx required. Uninterrupted use of high concentrations of oxygen over a long duration, without monitoring its effect on oxygen content of arterial blood, may be harmful. Do not attempt to use on patients who have stopped breathing unless used in conjunction with resuscitative equipment. Keep out of reach of children. Federal law requires that this container be refilled with oxygen USP only by establishments registered as a drug manufacturer in accordance with the Federal Food, Drug, and Cosmetic Act.
Produced by Air Liquefaction.
DANGER: MAY CAUSE OR INTENSIFY FIRE; OXIDIZER. CONTAINS REFRIGERATED GAS; MAY CAUSE CRYOGENIC BURNS OR INJURY. COMBUSTIBLES IN CONTACT WITH OXIDIZING REFRIGERATED LIQUIDS MAY EXPLODE ON IGNITION OR IMPACT. Obtain, read and follow all safety instructions before use. Keep away from clothing and other combustible materials. Keep valves and fittings free from grease and oil. Use and store only outdoors or in a well-ventilated place. Wear cold insulating gloves and either face shield or eye protection. In case of fire: Stop leak if safe to do so. Use a back flow preventive device in the piping. Close valve after each use and when empty. Use only with equipment rated for cylinder pressure. Do not open valve until connected to equipment prepared for use. Use only with equipment of compatible materials of construction. Open valve slowly. Use only with equipment cleaned for oxygen service. Always keep container in upright position. DO NOT change or force fit connections. Avoid spills. Do not walk on or roll equipment over spills. Read and follow the Safety Data Sheet (SDS) before use.
CAS: 7782-44-7
FIRST AID: IF ON SKIN: Immediately thaw frosted parts with lukewarm water. Do not rub affected area. Get medical help.
DO NOT REMOVE THIS PRODUCT LABEL
NO SMOKING
NO VAPING
O2 SAFE SOLUTIONS
Your Partner in Respiratory Care
O2 Safe Solutions
Technical Gas Products
101 N Plains Industrial Rd, Bldg 1B
Wallingford, CT 06492
1-800-847-0745